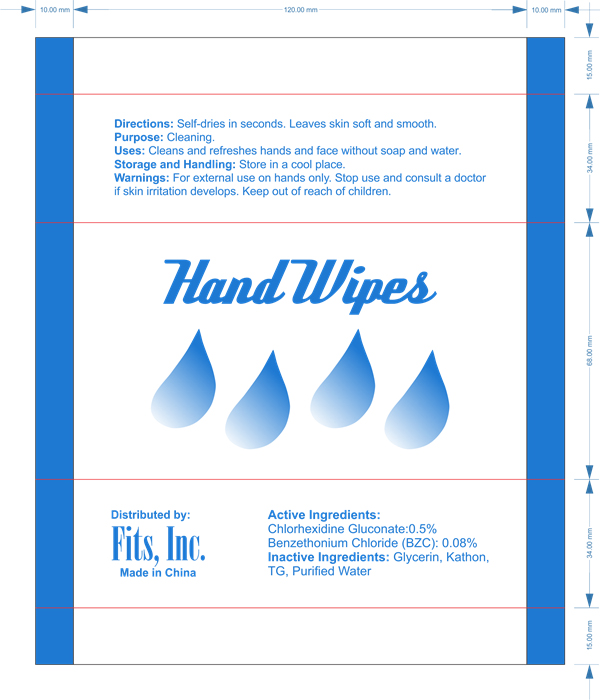 DRUG LABEL: Hand wipes
NDC: 61312-009 | Form: SWAB
Manufacturer: HANGZHOU GUOGUANG TOURING COMMODITY CO., LTD.
Category: otc | Type: HUMAN OTC DRUG LABEL
Date: 20180109

ACTIVE INGREDIENTS: CHLORHEXIDINE GLUCONATE 0.5 g/100 g; BENZALKONIUM CHLORIDE 0.08 g/100 g
INACTIVE INGREDIENTS: GLYCERIN; ALOE VERA LEAF; SODIUM DODECYLBENZENESULFONATE; WATER

61312-009 Hand wipes

Active ingredient

CHLORHEXIDINE GLUCONATE 0.5%

BENZALKONIUM CHLORIDE 0.08%

Purpose

Cleaning

Uses

Cleans and refreshes hands and face without soap and water

Warnings

For external use on hands only. Stop use and consult a doctor if skin irritation develops.
Keep out of reach of children.

Keep out of reach of children

Directions

Self-dries in seconds. Leaves skin soft and smooth.

INACTIVE INGREDIENT

Glycerin, Kathon, TG, Purified Water